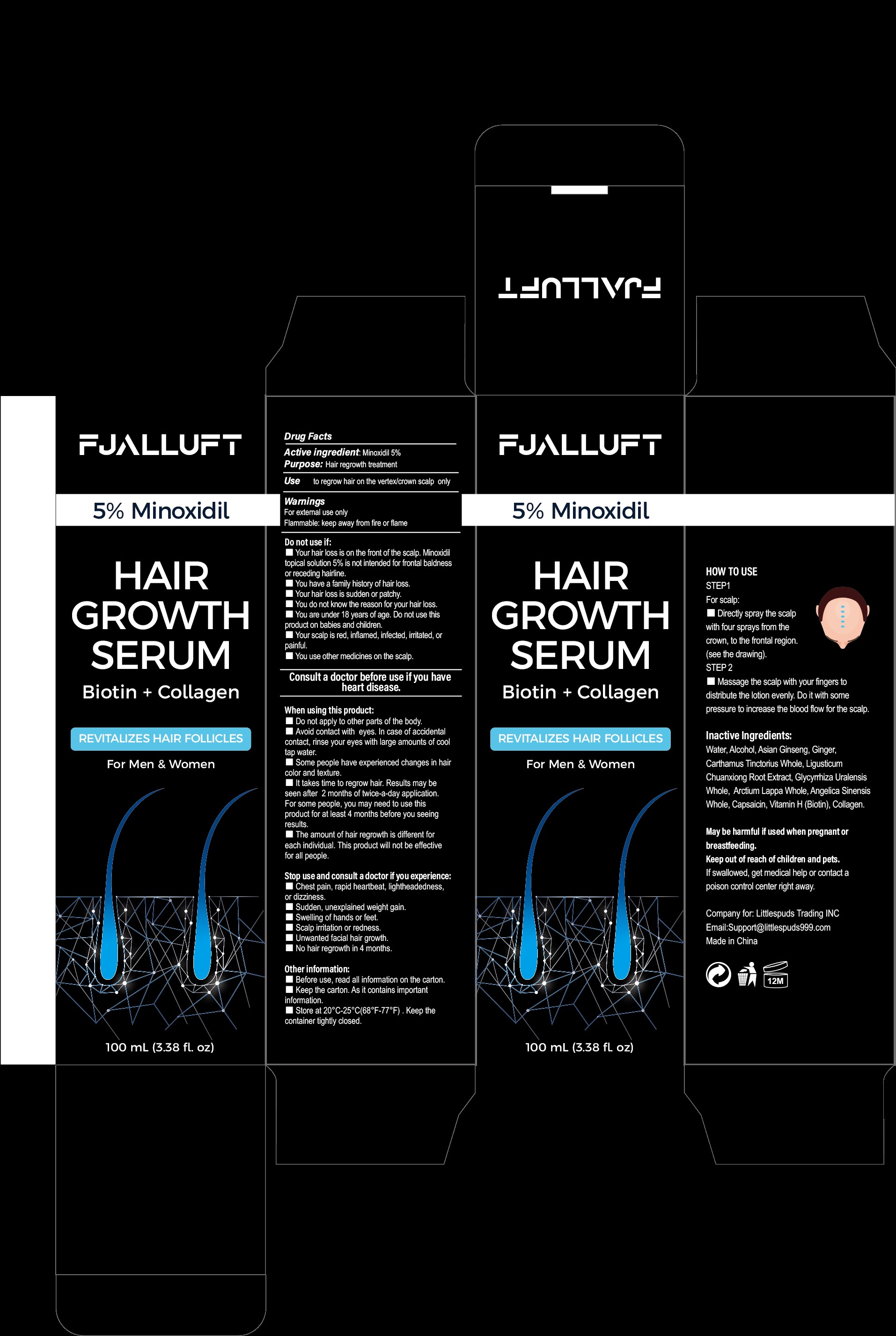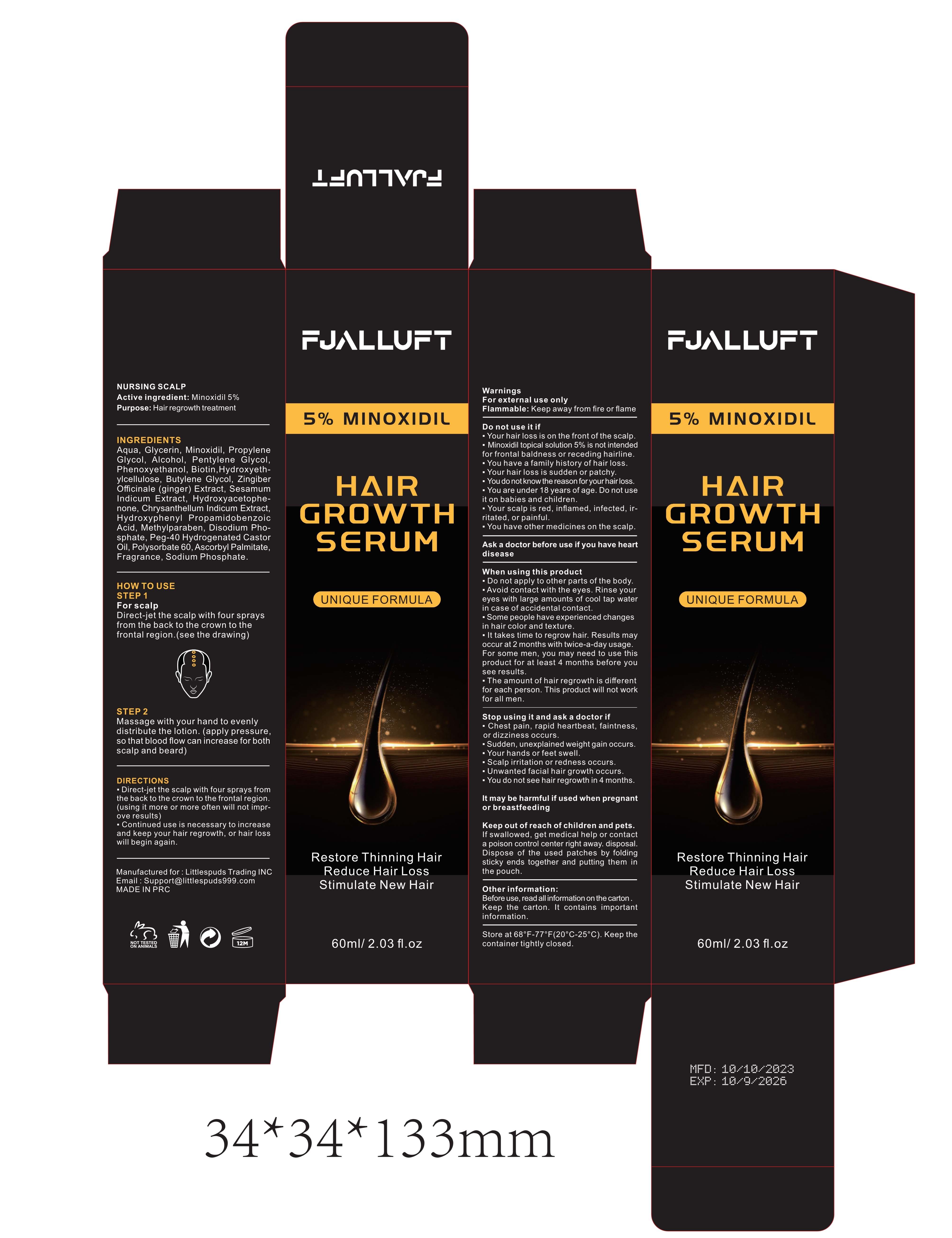 DRUG LABEL: Hair Growth Serum
NDC: 83563-001 | Form: SPRAY
Manufacturer: Fujian Oumao Electronic Commerce Co. , Ltd.
Category: otc | Type: HUMAN OTC DRUG LABEL
Date: 20231031

ACTIVE INGREDIENTS: MINOXIDIL 5 g/100 mL
INACTIVE INGREDIENTS: WATER; ALCOHOL

ACTIVE INGREDIENT

5% Minoxidil

ASK DOCTOR

Consult a doctor before use if you have heart disease!

Keep out of reach of children and pets.
If swallowed, get medical help or contact a poison control center right away.

PURPOSE

Hair regrowth treatment

Stop use and consult a doctor if you experience:
●Chest pain, rapid heartbeat, lightheadedness, or dizziness.
●Sudden, unexplained weight gain.
●Swelling of hands or feet.
●Scalp irritation or redness.
●Unwanted facial hair growth.
●No hair regrowth in 4 months.

When using this product:
● Do not apply to other parts of the body.
● Avoid contact with eyes. In case of accidental contact, rinse your eyes with large amounts of cool tap water.
● Some people have experienced changes in hair color and texture.
● It takes time to regrow hair. Results may be seen after 2 months of twice-a-day application. For some people, you may need to use this product for at least 4 months before seeing results.
● The amount of hair regrowth is different for each individual. This product will not be effective for all people.

Warnings
For external use only
Flammable: keep away from fire or flame

Other information:
●Before use, read all information on the carton .
●Keep the carton, as it contains important information.
●Store at 20°C-25°C (68°F-77°F). Keep the container tightly closed.
●May be harmful if used when pregnant or breastfeeding.

Inactive ingredients:
Water, Alcohol,Asian Ginseng,Ginger,Carthamus Tinctorius Whole ,Ligusticum Chuanxiong Root Extract,Glycyrrhiza Uralensis Whole,Arctium Lappa Whole,Angelica Sinensis Whole,Capsaicin , Vitamin H (Biotin) ,Collagen

INDICATIONS AND USAGE

Use to regrow hair on the vertex/crown scalp only.

DOSAGE AND ADMINISTRATION

HOW TO USE
STEP 1
For scalp
Directly spray the scalp with four sprays from the crown, to the frontal region
STEP 2
Massage the scalp with your fingers to distribute the lotion evenly. Do it with some pressure to increase the blood flow for the scalp